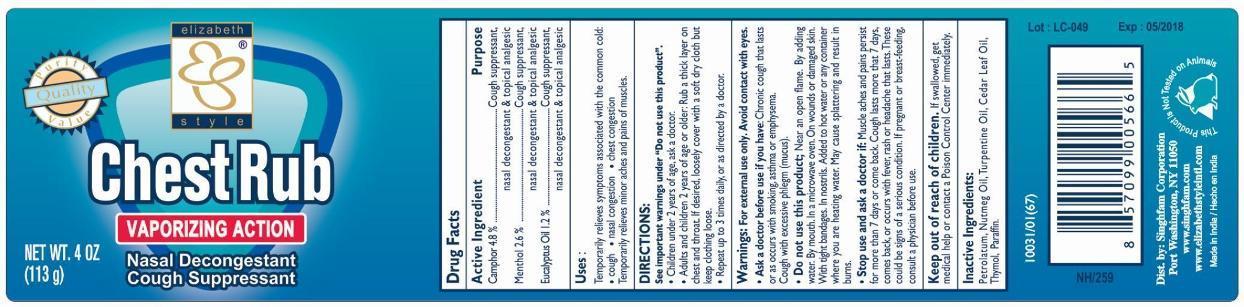 DRUG LABEL: Chest Rub
NDC: 52920-133 | Form: GEL
Manufacturer: Singhfam Corporation
Category: otc | Type: HUMAN OTC DRUG LABEL
Date: 20241219

ACTIVE INGREDIENTS: CAMPHOR (SYNTHETIC) 4.8 g/100 g; MENTHOL 2.6 g/100 g; EUCALYPTUS OIL 1.2 g/100 g
INACTIVE INGREDIENTS: PETROLATUM; NUTMEG OIL; TURPENTINE OIL; CEDAR LEAF OIL; THYMOL; PARAFFIN

Active Ingredients

Camphor 4.8%

Menthol 2.6%

Eucalyptus Oil 1.2%

Purpose

Cough Suppressant

Nasal Decongestant

Topical Analgesic

Uses

Temporarily releives symptoms associated with the common cold:

- cough
- nasal congestion
- chest congestion

Temporarily relives minor aches and pains of muscles.

Warnings

For external use only. Avoid contact with eyes.

Ask a doctor before use if you have,

- chronic cough that lasts or as occurs with smoking, asthma, or emphysema
- cough with excessive phlegm (mucus)

Do not use this product

- near an open flame
- by adding water
- by mouth
- in a microwave oven
- on wounds or damaged skin
- with tight bandages
- in nostrils
- added to hot water or any container where you are heating water
- may cause splattering and results in burns

Stop use and ask a doctor if:

- if muscle aches and pains persist for more than 7 days or come back
- cough lasts more than 7 days, comes back, or occurs with fever, rash or headache that lasts. These could be signs of a serious conditions
- if pregnant or breast-feeding, consult a physician before use.

Keep out of the reach of children

If swallowed, get medical help or contact a Poison Control Center immediately.

DOSAGE AND ADMINISTRATION

Directions: see important warnings under “Do not use this product”

children under 2 years of age, ask a doctor

adults and children 2 years of age or older:

- rub a thick layer on chest and throat
- if desired, loosely cover with a soft dry cloth but keep clothing loose
- repeat up to 3 times daily, or as directed by a doctor

Inactive Ingredients

Petrolatum, Nutmeg Oil, Turpentine Oil, Cedar Leaf Oil, Thymol, Parrafin.

PACKAGE LABEL

PRINCIPAL DISPLAY PANEL

CHEST RUB VAPORIZING ACTION GEL

NASAL DECONGESTANT AND COUGH SUPPRESSANT

NET WT. 4 OZ (113g)